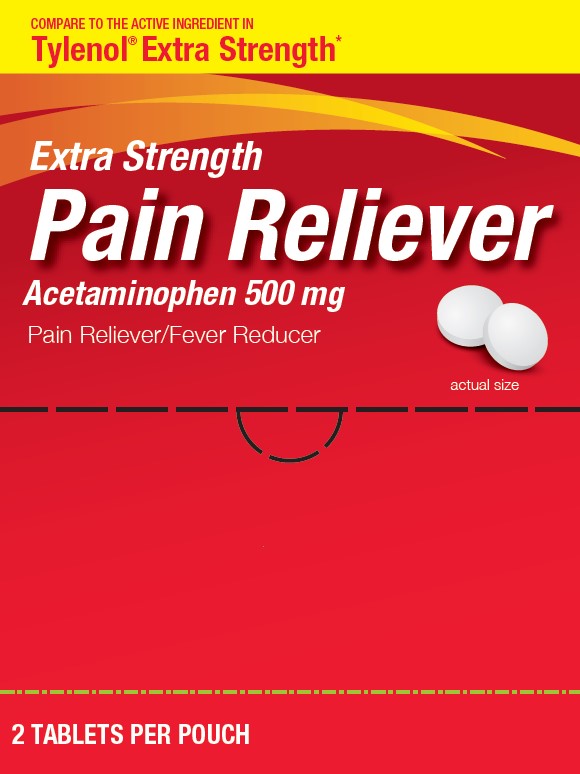 DRUG LABEL: Extra Strength Pain Reliever
NDC: 29485-9281 | Form: TABLET
Manufacturer: Lil' Drug Store Products, Inc.
Category: otc | Type: HUMAN OTC DRUG LABEL
Date: 20240619

ACTIVE INGREDIENTS: ACETAMINOPHEN 500 mg/1 1
INACTIVE INGREDIENTS: STARCH, CORN; HYPROMELLOSE, UNSPECIFIED; POVIDONE, UNSPECIFIED; SODIUM STARCH GLYCOLATE TYPE A CORN; MALTODEXTRIN; MICROCRYSTALLINE CELLULOSE; TITANIUM DIOXIDE; STEARIC ACID; POLYETHYLENE GLYCOL, UNSPECIFIED

Extra Strength Pain Reliever

Active Ingredient (in each tablet)

Acetaminophen 500 mg

Purpose

Pain reliever/fever reducer

USES

- temporarily relieves minor aches and pains due to:
- the common cold
- headache
- backache
- minor pain of arthritis
- toothache
- muscular aches
- premenstrual and menstrual cramps
- temporarily reduces fever

Warnings

Liver warning

This product contains acetaminophen. The maximum daily dose of this product is 6 tablets (3,000 mg) in 24 hours.

Severe liver damage may occur if you take

- more than 4,000 mg of acetaminophen in 24 hours
- with other drugs containing acetaminophen
- 3 or more alcoholic drinks every day while using this product.

Allergy alert

:acetaminophen may cause severe skin reactions. Symptoms may include:

- skin reddening
- blisters
- rash

If a skin reaction occurs, stop use and seek medical help right away.

Do not use

- with any other drug containing acetaminophen (prescription or nonprescription). If you are not sure whether a drug contains acetaminophen, ask a doctor or pharmacist.
- if you are allergic to acetaminophen or any of the inactive ingredients in this product

Ask a doctor before use if you have

liver disease

Ask a doctor before use if you are

taking the blood thinning drug warfarin

Stop use and ask a doctor if

- pain gets worse or lasts more than 10 days
- fever gets worse or lasts more than 3 days
- new symptoms occur
- redness or swelling is present

These could be signs of a serious condition.

If pregnant or breast-feeding,

ask a health professional before use.

Keep out of reach of children

Overdose warning

Taking more than the recommended dose (overdose) may cause liver damage. In case of overdose, get medical help or contact a Poison Control Center (1-800-222-1222) right away. Quick medical attention is critical for adults as well as for children even if you do not notice any signs or symptoms.

Directions

- do not take more than directed (see overdose warning)
  adults and children 12 years and over | - take 2 tablets every 6 hours while symptoms last - do not take more than 6 tablets in 24 hours, unless directed by a doctor - do not use for more than 10 days unless directed by a doctor
  children under 12 years | ask a doctor

Other Information

- do not use if inner pouch or carton is open or damaged
- store at room temperature 59-86˚F (15-30˚C)
- see bottom panel for lot number and expiration date

Inactive Ingredients

corn starch, hypromellose, maltodextrin [may contain] , microcrystalline cellulose , polyethylene glycol, povidone , pregelatinized starch , sodium starch glycolate , stearic acid, titanium dioxide

Questions or Comments?

call toll-free 1-800-351-2000 (M-F 8:00 AM-4:30 PM CST)

*This product is not manufactured or distributed by JOHNSON & JOHNSON, INC., McNeil Consumer Healthcare Division,

distributor of Tylenol® Extra Strength.

Manufactured for:

Lil' Drug Store products, Inc.

9300 Earhart Lane SW

Cedar Rapids, IA 52404

PACKAGE LABEL

COMPARE TO THE ACTIVE INGREDIENT IN

Tylenol® Extra Strength*

Extra Strength

Pain Reliever

Acetaminophen 500mg

Pain Reliever/Fever Reducer

actual size [pill image]

2 TABLETS PER POUCH